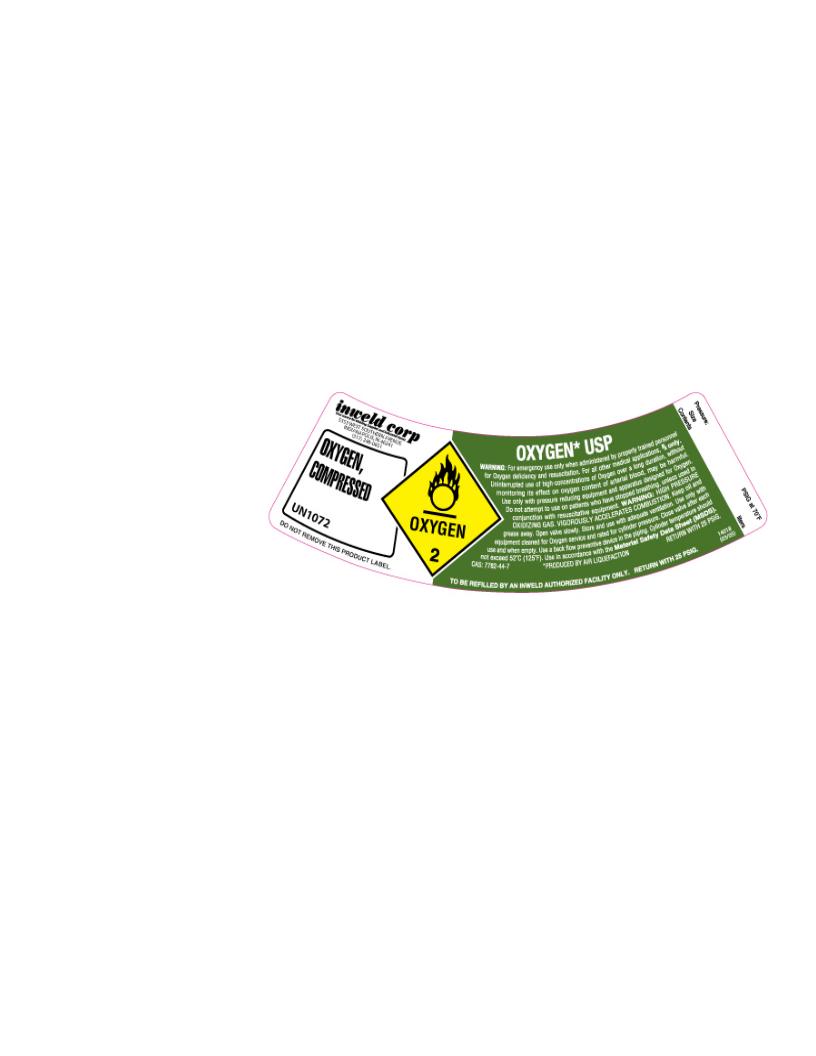 DRUG LABEL: Oxygen
NDC: 49778-001 | Form: GAS
Manufacturer: American Welding & Gas
Category: prescription | Type: HUMAN PRESCRIPTION DRUG LABEL
Date: 20100219

ACTIVE INGREDIENTS: Oxygen 992 mL/1000 mL

Compressed Oxygen Label

PACKAGE LABEL

OXYGEN,
COMPRESSED

UN1072

OXYGEN*, USP

WARNING: For emergency use only when administered by properly trained personnel for Oxygen deficiency and resuscitation. For all other medical applications, Rx Only. Uninterrupted use of high concentrations of Oxygen over a long duration, without monitoring its effect on oxygen content of arterial blood, may be harmful. Use only with pressure reducing equipment and apparatus designed for Oxygen. Do not attempt to use on patients who have stopped breathing, unless used in conjunction with resuscitative equipment.

WARNING: HIGH PRESSURE OXIDIZING GAS. VIGOROUSLY ACCELERATES COMBUSTION. Keep oil and grease away. Open valve slowly. Store and use with adequate ventilation. Use only with equipment cleaned for Oxygen service and rated for cylinder pressure. Close valve after each use and when empty. Use a back flow preventive device in the piping. Cylinder temperature should not exceed 52°C (125°F). Use in accordance with the Material Safety Data Sheet (MSDS).

*PRODUCED BY AIR LIQUEFACTION RETURN WITH 25 PSIG.
TO BE REFILLED BY AN INWELD AUTHORIZED FACILITY ONLY. RETURN WITH 25 PSIG.

Pressure: ___________ PSIG at 70°F
Size: _______________
Contents: ___________ Liters
DO NOT REMOVE THIS PRODUCT LABEL.